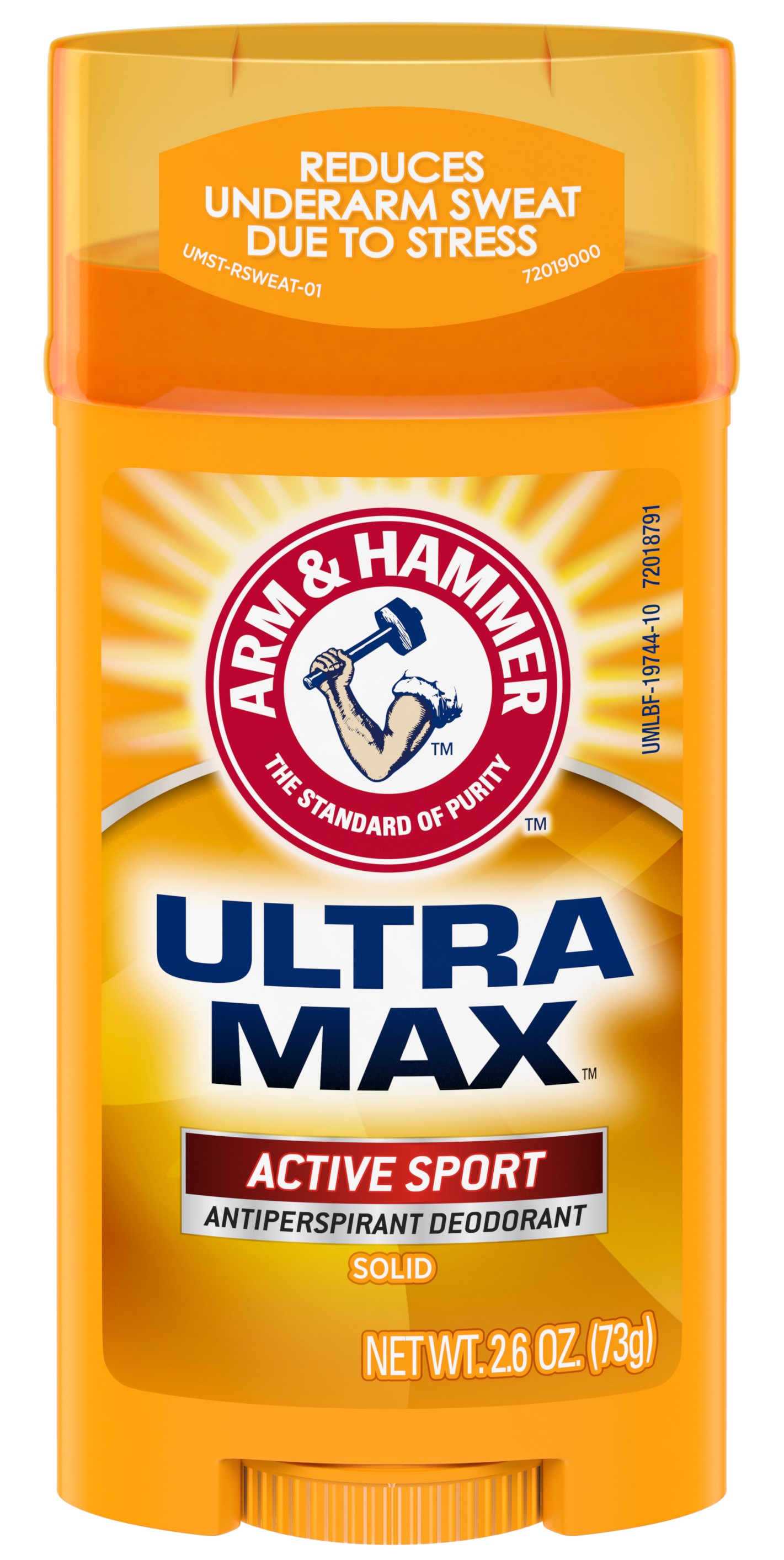 DRUG LABEL: UltraMax Invisible Solid - Active Sport
NDC: 10237-871 | Form: STICK
Manufacturer: Church & Dwight Co., Inc.
Category: otc | Type: HUMAN OTC DRUG LABEL
Date: 20241120

ACTIVE INGREDIENTS: ALUMINUM CHLOROHYDRATE 0.19 g/1 g
INACTIVE INGREDIENTS: CYCLOMETHICONE 5; PPG-14 BUTYL ETHER; STEARYL ALCOHOL; C12-20 ALKYL BENZOATE; HYDROGENATED CASTOR OIL; TALC; PETROLATUM; SODIUM BICARBONATE; STARCH, CORN; MALTODEXTRIN; XANTHAN GUM

Arm and Hammer UltraMax Invisible Solid - Active Sport

ACTIVE INGREDIENT

Aluminum Chlorohydrate 19%

PURPOSE

Antiperspirant

INDICATIONS AND USAGE

Usereduces underarm perspiration

WARNINGS

For external use only

Do not useon broken skin

Stop use ifrash or irritation occurs

Ask a doctor before use if you havekidney disease

Keep out of reach of children.If swallowed, get medical help or contact a Poison Control Center right away.

Directions

Apply a thin layer to underarms only

INACTIVE INGREDIENT

PPG-14 Butyl Ether, Cyclopentasiloxane, Stearyl Alcohol, C12-15 Alkyl Benzoate, Talc, Hydrogenated Castor Oil, Petrolatum, Fragrance, Sodium Bicarbonate (Baking Soda), Corn Starch Modified, Polysaccharides, Maltodextrin

Questions or Comments?

Call 1-800-248-8820

M-F 9am-5pm ET

or visit www.ahultramax.com

Principal Display

REDUCES

UNDERARM SWEAT

DUE TO STRESS

ARM AND HAMMER

THE STANDARD OF PURITY

ULTRA MAX

ACTIVE SPORT

ANTIPERSPIRANT DEODORANT

SOLID

NET WT. 2.6 OZ. (73g)